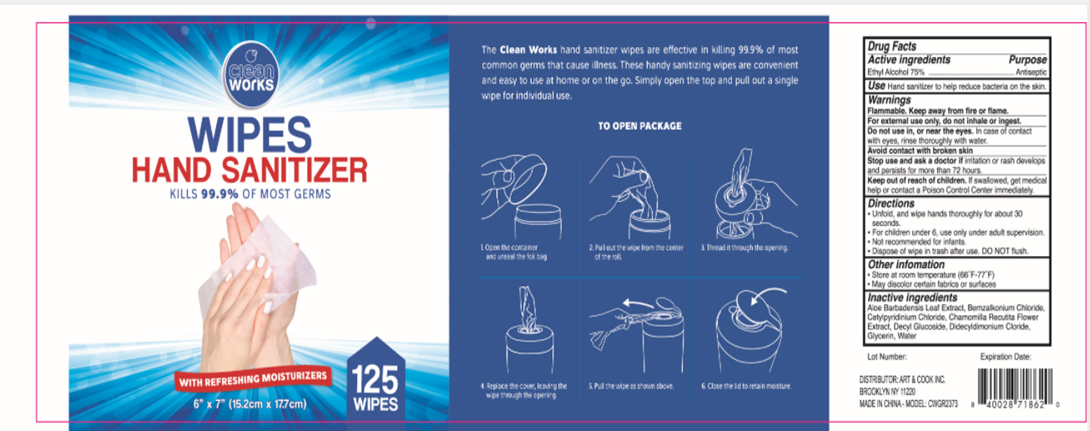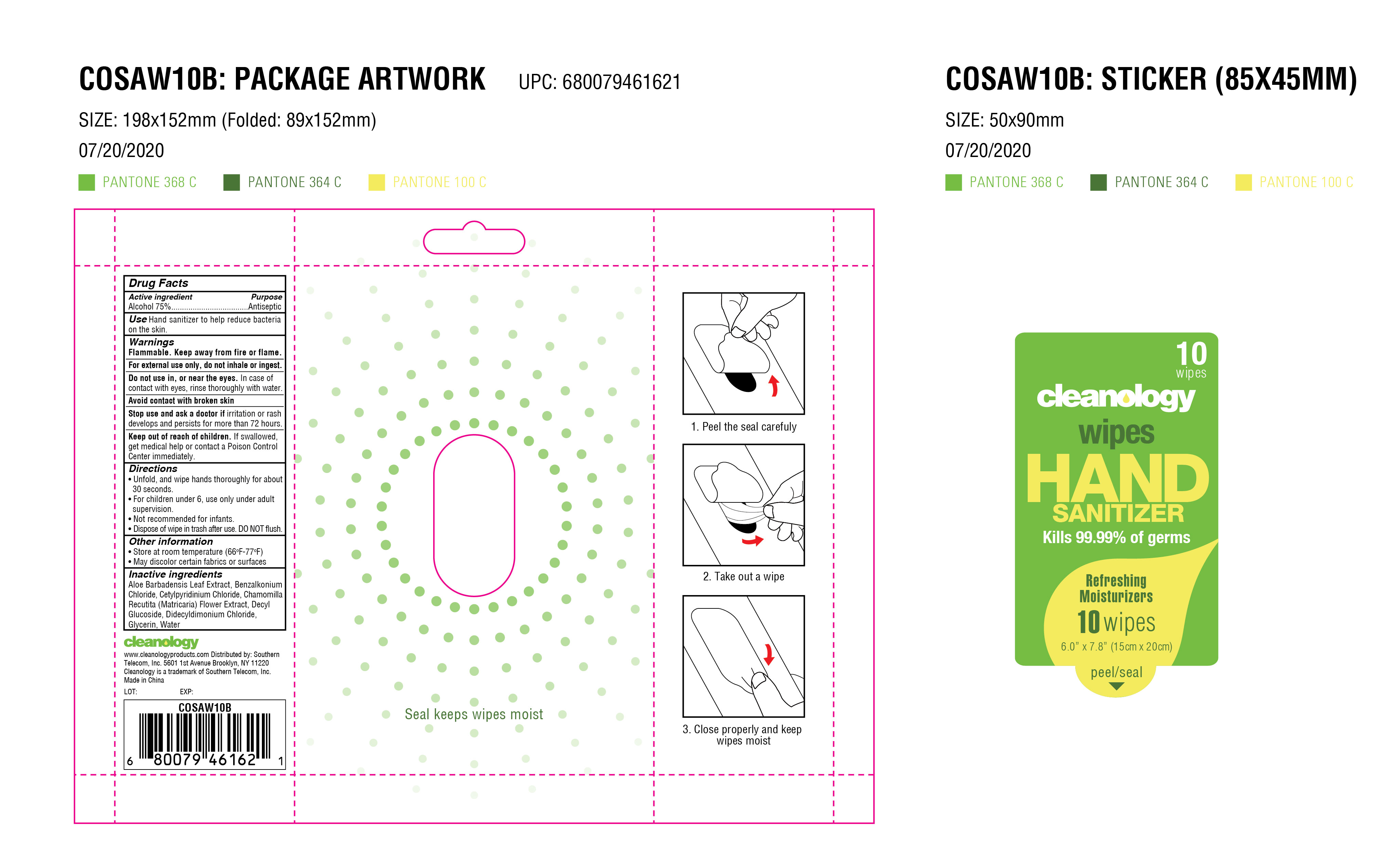 DRUG LABEL: sanitizing wipes
NDC: 42003-009 | Form: CLOTH
Manufacturer: Zhejiang jiayan daily commodity Co.,ltd
Category: otc | Type: HUMAN OTC DRUG LABEL
Date: 20200808

ACTIVE INGREDIENTS: ALCOHOL 0.75 mL/1 g
INACTIVE INGREDIENTS: CETYLPYRIDINIUM CHLORIDE; MATRICARIA RECUTITA FLOWERING TOP; DIDECYLDIMONIUM CHLORIDE; WATER; ALOE VERA LEAF; BENZALKONIUM CHLORIDE; DECYL GLUCOSIDE; GLYCERIN

sanitizing wipes

Active Ingredient(s)

Alcohol 75% v/v. Purpose: Antiseptic

Purpose

Antiseptic

Use

Hand sanitizer to help reduce bacteria on the skin.

Warnings

Flammable. Keep away from fire or flame.

For external use only, do not inhale or ingest.

Do not use in, or near the eyes. In case of contact with eyes, rinse thoroughly with water.

Avoid contact with broken skin

Stop use and ask a doctor if

irritation or rash develops and persists for more than 72 hours.

Keep out of reach of children. If swallowed, get medical help or contact a Poison Control Center immediately.

Directions

- Unfold, and wipe hands thoroughly for about 30 seconds.
- For children under 6, use only under adult supervision.
- Not recommeded for infants.
- Dispose of wipe in trash after use. DO NOT flush.

Other information

- Store at room temperature 66F-77F
- May discolor certain fabrics or surfaces

Inactive ingredients

aloe barbadensis leaf extract, benzalkonium chloride, cetylpyridinium chloride, chamomilla recutita flower extract , decyl glucoside, didecyldimonium chloride, glycerin, water

Package Label - Principal Display Panel

125 PCS NDC: 42003-009-01

Cleanworks

WIPES

HAND SAITIZER

KILLS 99.99% OF MOST GERMS

WITH REFRESHING MOISTURIZERS

6'' x 7' (15.2cm x 17.7cm)

125 WIPES

10 PCS NDC: 42003-009-02

cleanology

wipes

HAND

SANITIZER

Kills 99.99% of germs

Refreshing

Moisturizers

10 wipes

6.0'' x 7.8'' (15cm x 20cm)

Seel keeps wipes moist